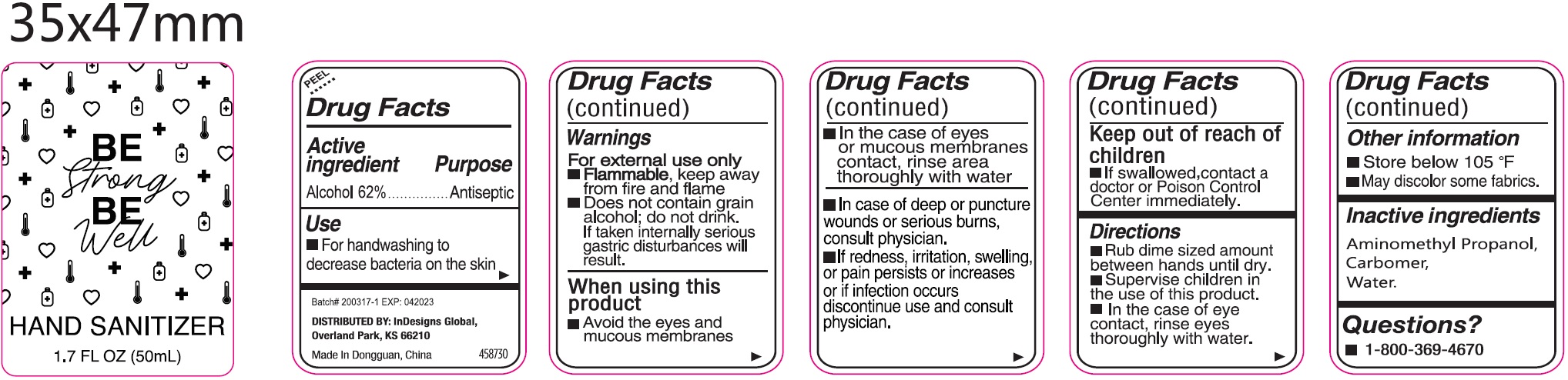 DRUG LABEL: Hand Sanitizer
NDC: 74712-000 | Form: GEL
Manufacturer: In Designs Global LLC
Category: otc | Type: HUMAN OTC DRUG LABEL
Date: 20231025

ACTIVE INGREDIENTS: ALCOHOL 0.62 mL/1 mL
INACTIVE INGREDIENTS: AMINOMETHYLPROPANOL; CARBOMER HOMOPOLYMER, UNSPECIFIED TYPE; WATER

Hand Sanitizer

Active ingredient

Alcohol 62%

Purpose

Antiseptic

Use

- For handwashing to decrease bacteria on the skin

Warnings

For external use only

- keep away from fire and flame Flammable,
- Does not contain grain alcohol; do not drink. If taken internally serious gastric disturbances will result.

When using this product

- Avoid the eyes and mucous membranes
- In the case of eyes or mucous membranes contact, rinse area thoroughly with water
- In case of deep or punture wounds or serious burns, consult physician.
- If redness, irritation, swelling, or pain persists or increases or if infection occurs discontinue use and physician.

Keep out of reach of children

- If swallowed, contact a doctor or Poison Control Center immediately.

Directions

- Rub dime sized amount between hands until dry.
- Supervise children in the use of this product.
- In the case of eye contact, rinse eyes thoroughly with water.

Other information

- Store below 105 °F
- May discolor some fabrics.

Inactive ingredients

Aminomethyl Propanol, Carbomer, Water.

Questions?

- 1-800-369-4670